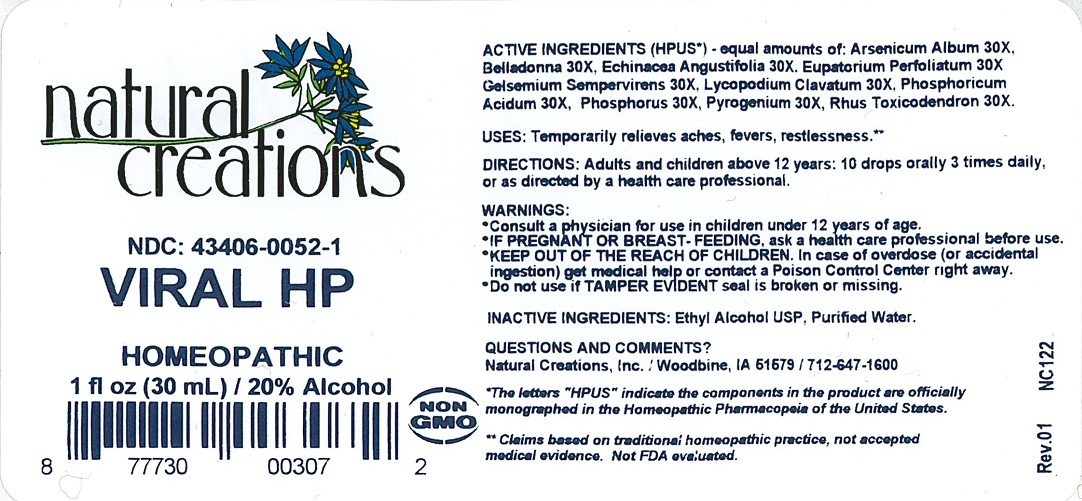 DRUG LABEL: VIRAL HP
NDC: 43406-0052 | Form: LIQUID
Manufacturer: Natural Creations, Inc.
Category: homeopathic | Type: HUMAN OTC DRUG LABEL
Date: 20251218

ACTIVE INGREDIENTS: ATROPA BELLADONNA 30 [hp_X]/1 mL; ECHINACEA ANGUSTIFOLIA 30 [hp_X]/1 mL; EUPATORIUM PERFOLIATUM FLOWERING TOP 30 [hp_X]/1 mL; GELSEMIUM SEMPERVIRENS ROOT 30 [hp_X]/1 mL; LYCOPODIUM CLAVATUM SPORE 30 [hp_X]/1 mL; PHOSPHORIC ACID 30 [hp_X]/1 mL; PHOSPHORUS 30 [hp_X]/1 mL; RANCID BEEF 30 [hp_X]/1 mL; TOXICODENDRON PUBESCENS LEAF 30 [hp_X]/1 mL; ARSENIC TRIOXIDE 30 [hp_X]/1 mL
INACTIVE INGREDIENTS: WATER; ALCOHOL

VIRAL HP

ACTIVE INGREDIENT

ACTIVE INGREDIENTS (HPUS*) - equal amounts of: Arsenicum Album 30X, Belladonna 30X, Echinacea Angustifolia 30X, Eupatorium Perfoliatum 30X, Gelsemium Sempervirens 30X, Lycopodium Clavatum 30X, Phosphoricum Acidum 30X, Phosphorus 30X, Pyrogenium 30X, Rus Toxicodendron 30X

INDICATIONS AND USAGE

USES: Temporarily relieves aches, fevers, restlessness.**

WARNING:

- Consult a physician for use in children under 12 years of age.
- IF PREGNANT OR BREAST-FEEDING, ask a health care professional before use.
- KEEP OUT OF THE REACH OF CHILDREN. In case of overdose (or accidental ingestion) get medical help or contact a Poison Control Center right away.
- Do not use if TAMPER EVIDENT seal is broken or missing.

DOSAGE AND ADMINISTRATION

DIRECTIONS: Adults and children above 12 years: 10 drops orally 3 times daily, or as directed by a health care professional.

REFERENCES

*The letters "HPUS" indicate the components in the product are officially monographed in the Homeopathic Pharmacopeia of the United States.

**Claims based on traditional homeopathic practice, not accepted medical evidence. Not FDA evaluated.

INACTIVE INGREDIENTS: Ethyl Alcohol USP, Purified Water.

QUESTIONS AND COMMENTS?

Natural Creations / Woodbine, IA 51579 / 712-647-1600

PURPOSE

USES: Temporarily relieves aches, fevers, restlessness.**

KEEP OUT OF THE REACH OF CHILDREN.

PACKAGE LABEL

NDC: 43406-0052-1

VIRAL HP

HOMEOPATHIC

1 fl oz (30 mL) / 20% Alcohol

UPC: 877730003072